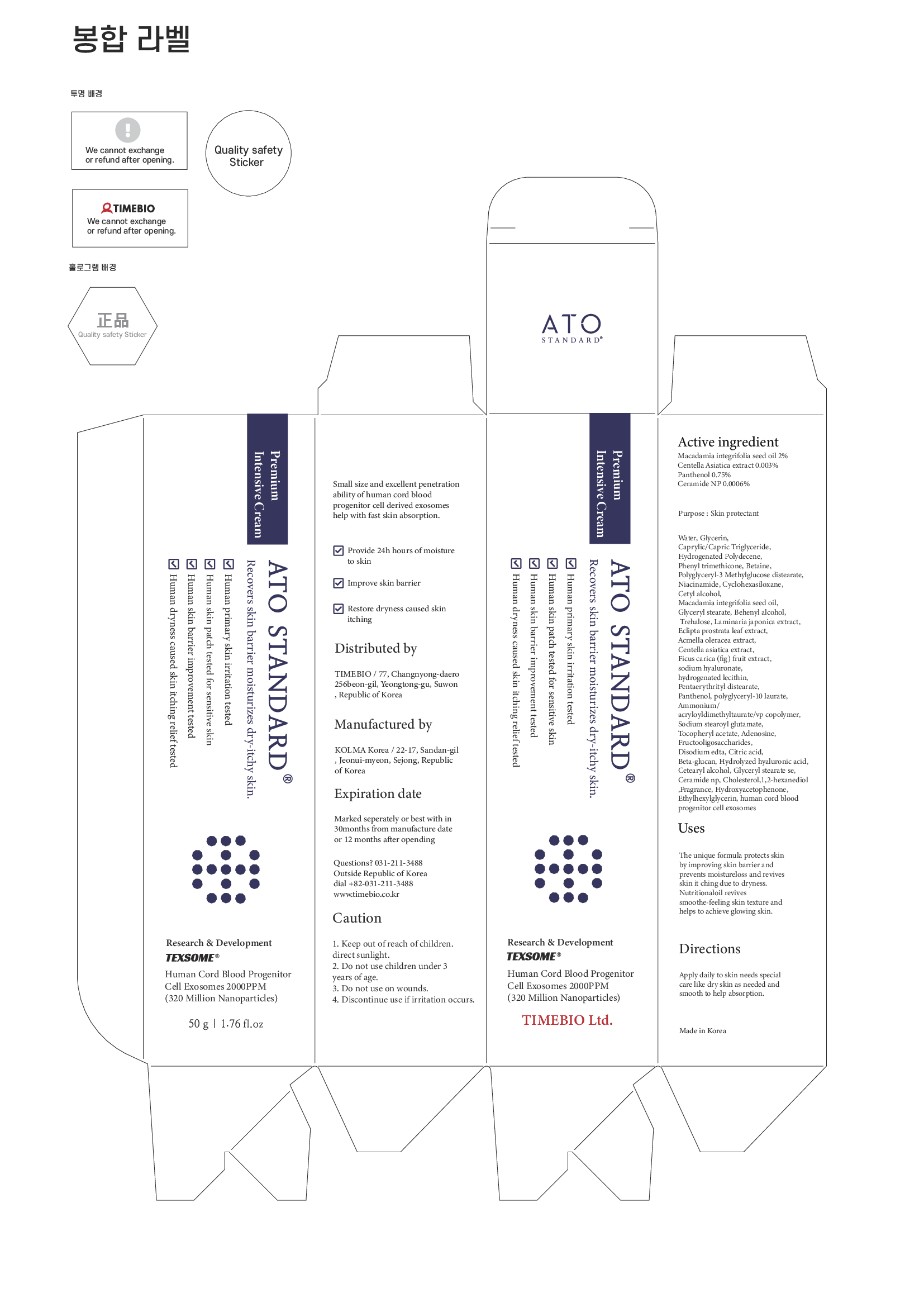 DRUG LABEL: ATO STANDARD INTENSIVECREAM
NDC: 81160-202 | Form: CREAM
Manufacturer: TIMEBIO Co., Ltd
Category: otc | Type: HUMAN OTC DRUG LABEL
Date: 20211123

ACTIVE INGREDIENTS: MACADAMIA OIL 2 g/100 g; CERAMIDE NP 0.0006 g/100 g; PANTHENOL 0.75 g/100 g; CENTELLA ASIATICA WHOLE 0.003 g/100 g
INACTIVE INGREDIENTS: EDETATE DISODIUM ANHYDROUS; CITRIC ACID MONOHYDRATE; GLYCERYL STEARATE SE; CHOLESTEROL; 1,2-HEXANEDIOL; HYDROXYACETOPHENONE; LAMINARIA JAPONICA; HYALURONATE SODIUM; POLYGLYCERYL-10 LAURATE; AMMONIUM ACRYLOYLDIMETHYLTAURATE/VP COPOLYMER; .ALPHA.-TOCOPHEROL ACETATE; CETOSTEARYL ALCOHOL; CETYL ALCOHOL; HYDROGENATED POLYDECENE (1500 CST); DOCOSANOL; ACMELLA OLERACEA FLOWERING TOP; PENTAERYTHRITYL DISTEARATE; WATER; MEDIUM-CHAIN TRIGLYCERIDES; PHENYL TRIMETHICONE; BETAINE; GLYCERIN; POLYGLYCERYL-3 METHYLGLUCOSE DISTEARATE; CYCLOMETHICONE 6; ETHYLHEXYLGLYCERIN; NIACINAMIDE; GLYCERYL MONOSTEARATE; TREHALOSE; ECLIPTA PROSTRATA LEAF; FIG; HYDROGENATED SOYBEAN LECITHIN; SODIUM STEAROYL GLUTAMATE; ADENOSINE

81160-202 ATO STANDARD INTENSIVE CREAM

Active Ingredient

MACADAMIA INTEGRIFOLIA SEED OIL 2%

CENTELLA ASIATICA EXTRACT 0.003%

PANTHENOL 0.75%

CERAMIDE NP 0.0006%

Purpose

Skin protectant

Uses

The unique formula protects skin by improving skin barrier and prevents moistureloss and revives skin itching due to dryness.

Nutritional oil revives smoothe-feeling skin texture and helps to achieve glowing skin.

Warnings

Direct sunlight.

Do not use children under 3 years of age

Do not use on wounds

Warnings

Discontinue use if irritation occurs.

Warnings

Keep out of reach of children.

Directions

Apply daily to skin needs special care like dry skin as needed and smooth to help absorption.

Inactive Ingredient

WATER, GLYCERIN, CAPRYLIC/CAPRIC TRIGLYCERIDE, HYDROGENATED POLYDECENE, PHENYL TRIMETHICONE, BETAINE, POLYGLYCERYL-3 METHYLGLUCOSE DISTEARATE, NIACINAMIDE, CYCLOHEXASILOXANE, CETYL ALCOHOL, GLYCERYL STEARATE, BEHENYL ALCOHOL, TREHALOSE, LAMINARIA JAPONICA EXTRACT, ECLIPTA PROSTRATA LEAF EXTRACT, ACMELLA OLERACEA EXTRACT, FICUS CARICA (FIG) FRUIT EXTRACT, SODIUM HYALURONATE, HYDROGENATED LECITHIN, WATER (and) HUMAN CORD BLOOD PROGENITOR CELL EXOSOMES, PENTAERYTHRITYL DISTEARATE, POLYGLYCERYL-10 LAURATE, AMMONIUM ACRYLOYLDIMETHYLTAURATE/VP COPOLYMER, SODIUM STEAROYL GLUTAMATE, TOCOPHERYL ACETATE, ADENOSINE, FRUCTOOLIGOSACCHARIDES, DISODIUM EDTA, CITRIC ACID, BETA-GLUCAN, HYDROLYZED HYALURONIC ACID, CETEARYL ALCOHOL, GLYCERYL STEARATE SE, CHOLESTEROL, 1,2-HEXANEDIOL, FRAGRANCE, HYDROXYACETOPHENONE, ETHYLHEXYLGLYCERIN